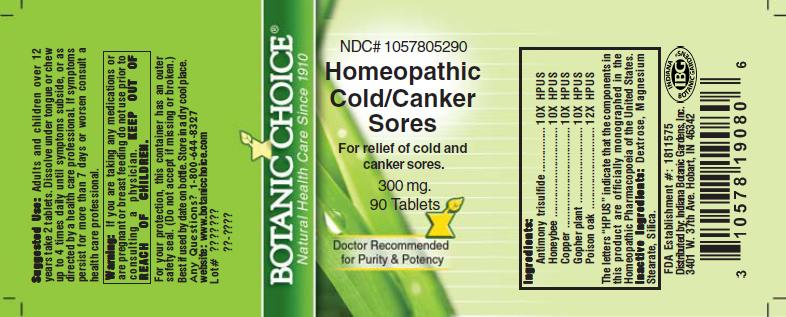 DRUG LABEL: Homeopathic Cold and Canker Sore Formula
NDC: 10578-052 | Form: TABLET
Manufacturer: Indiana Botanic Gardens
Category: homeopathic | Type: HUMAN OTC DRUG LABEL
Date: 20110325

ACTIVE INGREDIENTS: ANTIMONY TRISULFIDE 10 [hp_X]/1 1; APIS MELLIFERA 10 [hp_X]/1 1; COPPER 10 [hp_X]/1 1; EUPHORBIA LATHYRIS 10 [hp_X]/1 1; TOXICODENDRON PUBESCENS LEAF 12 [hp_X]/1 1
INACTIVE INGREDIENTS: DEXTROSE; MAGNESIUM STEARATE ; SILICON DIOXIDE 

Homeopathic Cold and Canker Sore Formula

ACTIVE INGREDIENT

I n g r e d i e n t s :

Antimony trisulfide........................ 10X HPUS
Honeybee................................. 10X HPUS
Copper.......................... 10X HPUS
Gopher plant...........................10X HPUS
Poison oak........................ 12X HPUS

The letters “HPUS” indicate that the components in
this product are officially monographed in the
Homeopathic Pharmacopoeia of the United States.

PURPOSE

For relief of cold and canker sores

KEEP OUT OF
REACH OF CHILDREN.

INDICATIONS AND USAGE

For relief of cold and canker sores

WARNINGS

Warning: If you are taking any medications or
are pregnant or breast feeding do not use prior to
consulting a physician.

DOSAGE AND ADMINISTRATION

Suggested Use: Adults and children over 12
years, take 2 tablets. Dissolve under tongue or
chew up to 4 times daily until symptoms subside,
or as directed by a health professional. If
symptoms persist for more than 7 days or worsen consult a
health professional.

Inactive Ingredients: Dextrose, Magnesium
Stearate, Silica.

PACKAGE LABEL

NDC# 1057805290

Homeopathic Cold and Canker Sore Formula

For relief of cold and canker sores

300 mg.
90 Tablets

USER SAFETY WARNINGS

For your protection, this container has an outer
safety seal. (Do not accept if missing or broken.)
Best if used by date on bottle. Store in a dry cool place.
Any Questions? 1-800-644-8327
website: www.botanicchoice.com

FDA Establishment #: 1811575

Distributed by: Indiana Botanic Gardens, Inc.
3401 W. 37th Ave. Hobart, IN 46342